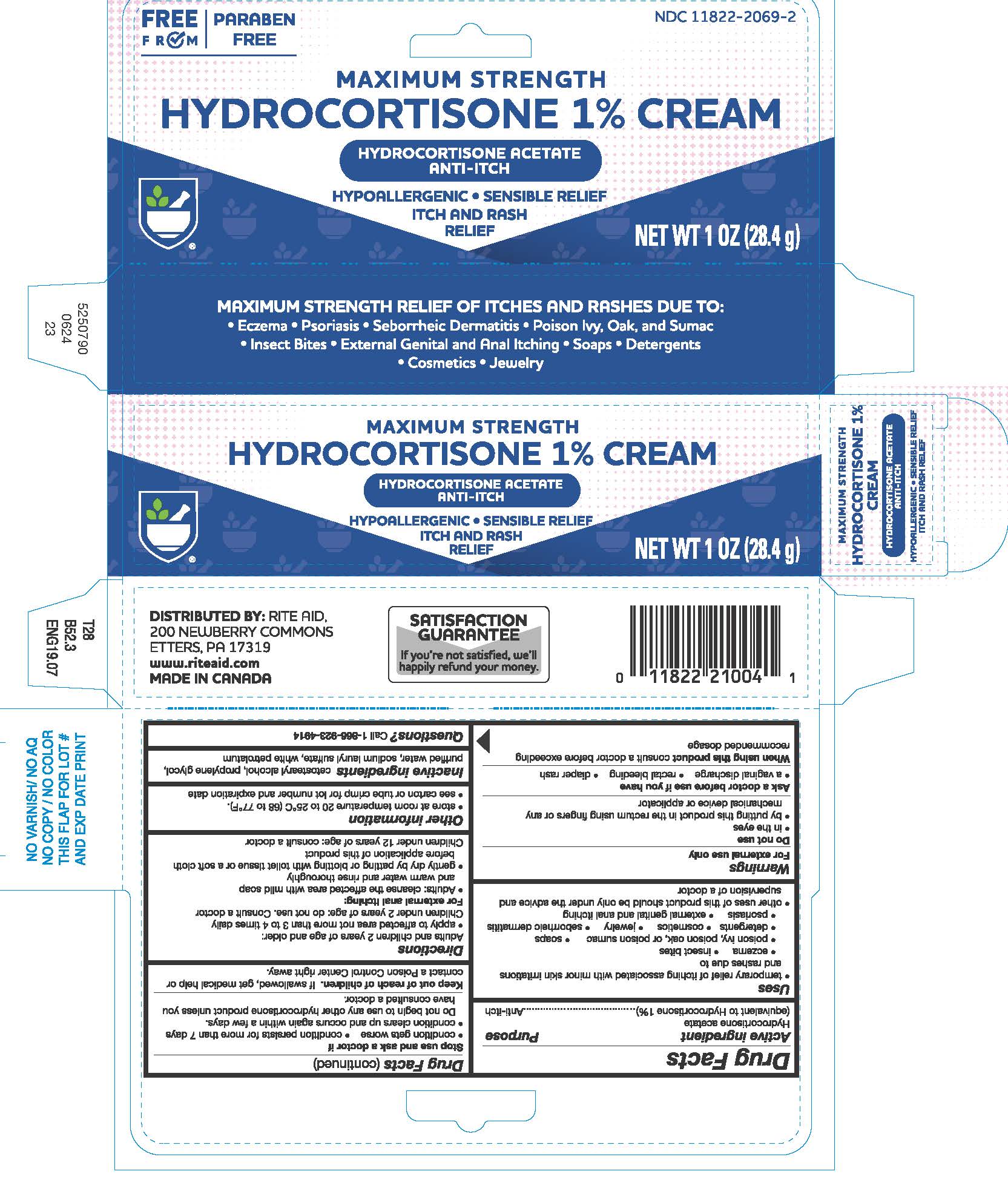 DRUG LABEL: Hydrocortisone
NDC: 11822-2069 | Form: CREAM
Manufacturer: Rite Aid Corporation
Category: otc | Type: HUMAN OTC DRUG LABEL
Date: 20250711

ACTIVE INGREDIENTS: HYDROCORTISONE ACETATE 1 g/100 g
INACTIVE INGREDIENTS: SODIUM LAURYL SULFATE; WATER; CETOSTEARYL ALCOHOL; PETROLATUM; PROPYLENE GLYCOL

Hydrocortisone 1% Cream

Drug Facts

Active ingredient

Hydrocortisone acetate (equivalent to Hydrocortisone 1%)

Purpose

Anti-itch cream

Uses

- temporary relief of itching associated with minor skin irritations and rashes due to
  - eczema
  - insect bites
  - poison ivy, poison oak, or poison sumac
  - soaps
  - detergents
  - cosmetics
  - jewelry
  - seborrheic dermatitis
  - psoriasis
  - external genital and anal itching
- other uses of this product should be only under the advice and supervision of a doctor

Warnings

For external use only

Do not use

- in the eyes
- by putting this product into the rectum by using fingers or any mechanical device or applicator

Ask a doctor before use if you have

- a vaginal discharge
- rectal bleeding
- diaper rash

WHEN USING

When using this productconsult a doctor before exceeding recommended dosage

Stop use and ask a doctor if

- condition gets worse
- condition persists for more than 7 days
- condition clears up and occurs again within a few days.

Do not begin to use any other hydrocortisone product unless you have consulted a doctor.

Keep out of reach of children.If swallowed, get medical help or contact a Poison Control Center right away.

Directions

Adults and children 2 years of age and older:

- apply to affected area not more than 3 to 4 times daily

Children under 2 years of age: do not use. Consult a doctor

For external anal itching:

- Adults: when practical, cleanse the affected area with mild soap and warm water and rinse thoroughly
- gently dry by patting or blotting with toilet tissue or a soft cloth before application of this product

Children under 12 years of age: consult a doctor

Other information

- store at room temperature
- see carton or tube crimp for lot number and expiration date

Inactive ingredients

cetostearyl alcohol, propylene glycol, purified water, sodium lauryl sulfate, white petrolatum

Questions?

Call 1-866-923-4914

DISTRIBUTED BY:
RITE AID, 30 HUNTER LANE,
CAMP HILL, PA 17011

PRINCIPAL DISPLAY PANEL - 28.4 g Tube Carton

MAXIMUM STRENGTH
HYDROCORTISONE 1% CREAM

HYDROCORTISONE ACETATE
ANTI-ITCH

HYPOALLERGENIC
ITCH AND RASH
RELIEF

NET WT 1 OZ (28.4 g)